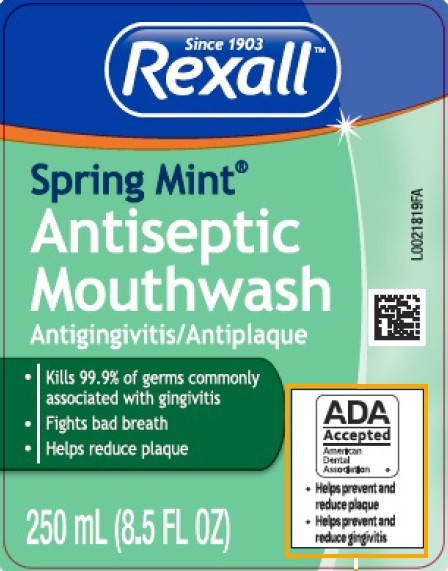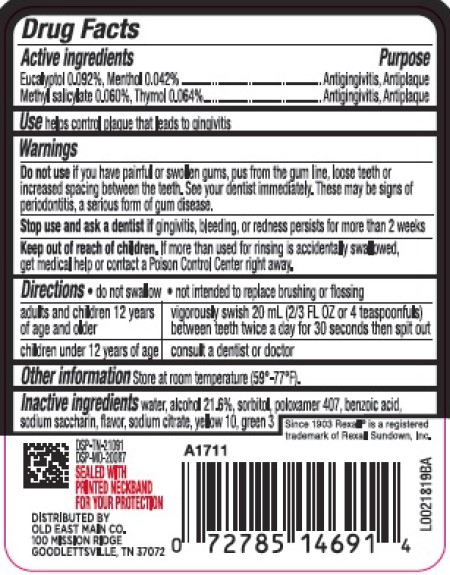 DRUG LABEL: Antispetic
NDC: 55910-099 | Form: MOUTHWASH
Manufacturer: Old East Main Co.
Category: otc | Type: HUMAN OTC DRUG LABEL
Date: 20260302

ACTIVE INGREDIENTS: EUCALYPTOL 0.92 mg/1 mL; MENTHOL 0.42 mg/1 mL; METHYL SALICYLATE 0.6 mg/1 mL; THYMOL 0.64 mg/1 mL
INACTIVE INGREDIENTS: WATER; ALCOHOL; SORBITOL; POLOXAMER 407; BENZOIC ACID; SACCHARIN SODIUM; SODIUM CITRATE; D&C YELLOW NO. 10; FD&C GREEN NO. 3

Rexall 072.002/072AL rev 2 - 072AN
Spring Mint Antiseptic Mouthrinse

Active ingredients

Eucalyptol 0.092%

Menthol 0.042%

Methyl sailcylate 0.060%

Thymol 0.064%

Purpose

Antigingivitis, Antiplaque

Use

helps control plaque that leads to gingivitis

Warnings

Warnings for this product

Do not use

if you have painful or swollen gums, pus from the gum line, loose teeth or increased spacing between the teeth. See your dentist immediately. These may be signs of periodontitis, a serious form of gum disease.

Stop use and ask a dentist if

gingivitis, bleeding, or redness persists for more than 2 weeks.

Keep out of reach of children.

If more than used for rinsing is accidentally swallowed, get medical help or contact a Poison Control Center right away.

Directions

- do not swallow
- not intended to replace brushing or flossing

adults and children under 12 years if age and older - vigorously swish 20 ml (2/3 FL OZ or 4 teaspoonfuls) between teeth twice a day for 30 seconds then spit out

children under 12 years of age - consult a dentist or doctor

other information

Store at room temperature (59⁰ - 77⁰ F).

Inactive ingredients

water, alcohol 21.6 %, sorbitol, flavor, poloxamer 407, benzoic acid, sodium saccharin, flavor, sodium citrate, yellow 10, green 3

ADVERSE REACTIONS

Since 1903 Rexall® is a registered trademark of Rexall Sundown, Inc.

DSP-TN-21091

DSP-MO-20087

SEALED WITH PRINTED NECKBAND FOR YOUR PROTECTION

DISTRIBUTED BY

OLD EAST MAIN CO.

100 MISSION RIDGE

GOOLETTSVILLE, TN 37072

principal display panel

Since 1903

Rexall™

Spring Mint®

Antiseptic Mouthwash

Antigingivitis/Antiplaque

- Kills 99.9% of germs commonly assoicated with gingivitis
- Fights bad breath
- helps reduce plaque

ADA Accepted

America Dental Association

- Helps prevent and reduce plaque
- Helps prevent and reduce gingivitis

250 mL (8.5 FL OZ)